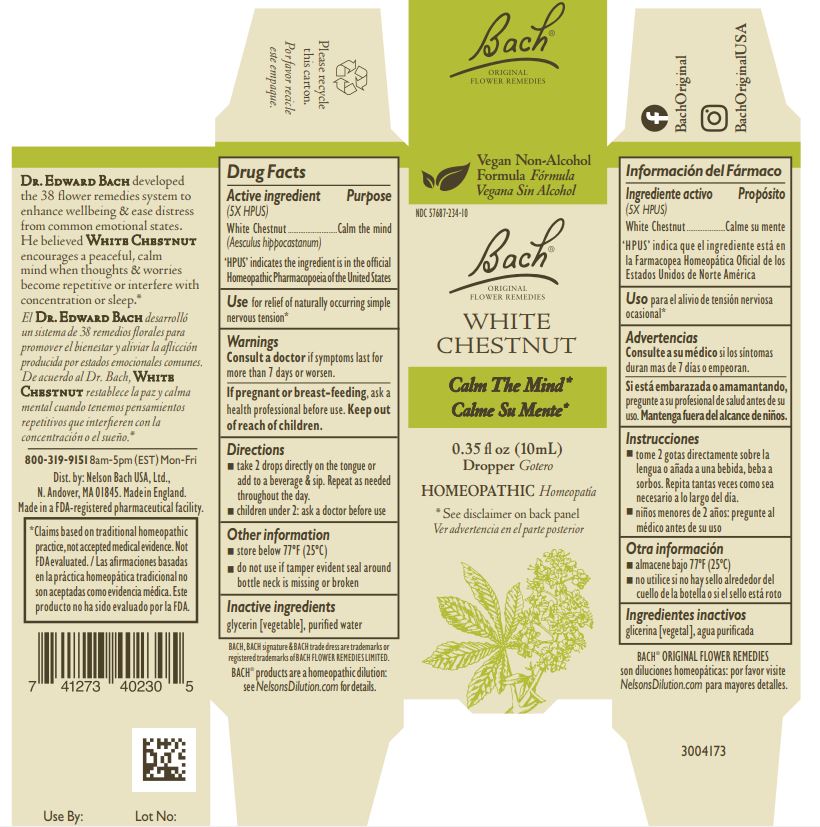 DRUG LABEL: Bach Original Flower Remedies White Chestnut
NDC: 57687-234 | Form: SOLUTION
Manufacturer: Nelson Bach USA Limited
Category: homeopathic | Type: HUMAN OTC DRUG LABEL
Date: 20221005

ACTIVE INGREDIENTS: AESCULUS HIPPOCASTANUM FLOWER 5 [hp_X]/0.095 mL
INACTIVE INGREDIENTS: WATER; GLYCERIN

Bach Original Flower Remedies White Chestnut

Active ingredient

White Chestnut (Aesculus hippocastanum) 5X HPUS

‘HPUS’ indicates the ingredient is in the official Homeopathic Pharmacopoeia of the United States

Purpose

Calm the mind

Use

For relief of naturally occurring simple nervous tension

Warnings

Consult a doctor if symptoms last for more than 7 days or worsen.

Keep out of reach of children.

PREGNANCY OR BREAST FEEDING

If pregnant or breast-feeding, ask a health professional before use.

Directions

Take 2 drops directly on the tongue or add to a beverage & sip. Repeat as needed throughout the day.

Children under 2: ask a doctor before use.

Other information

Store below 77 ºF (25 ºC)

Do not use if tamper evident seal around bottle neck is missing or broken

Inactive ingredients

glycerin [vegetable], purified water

Questions

800-319-9151 8am-5pm (EST) Mon-Fri